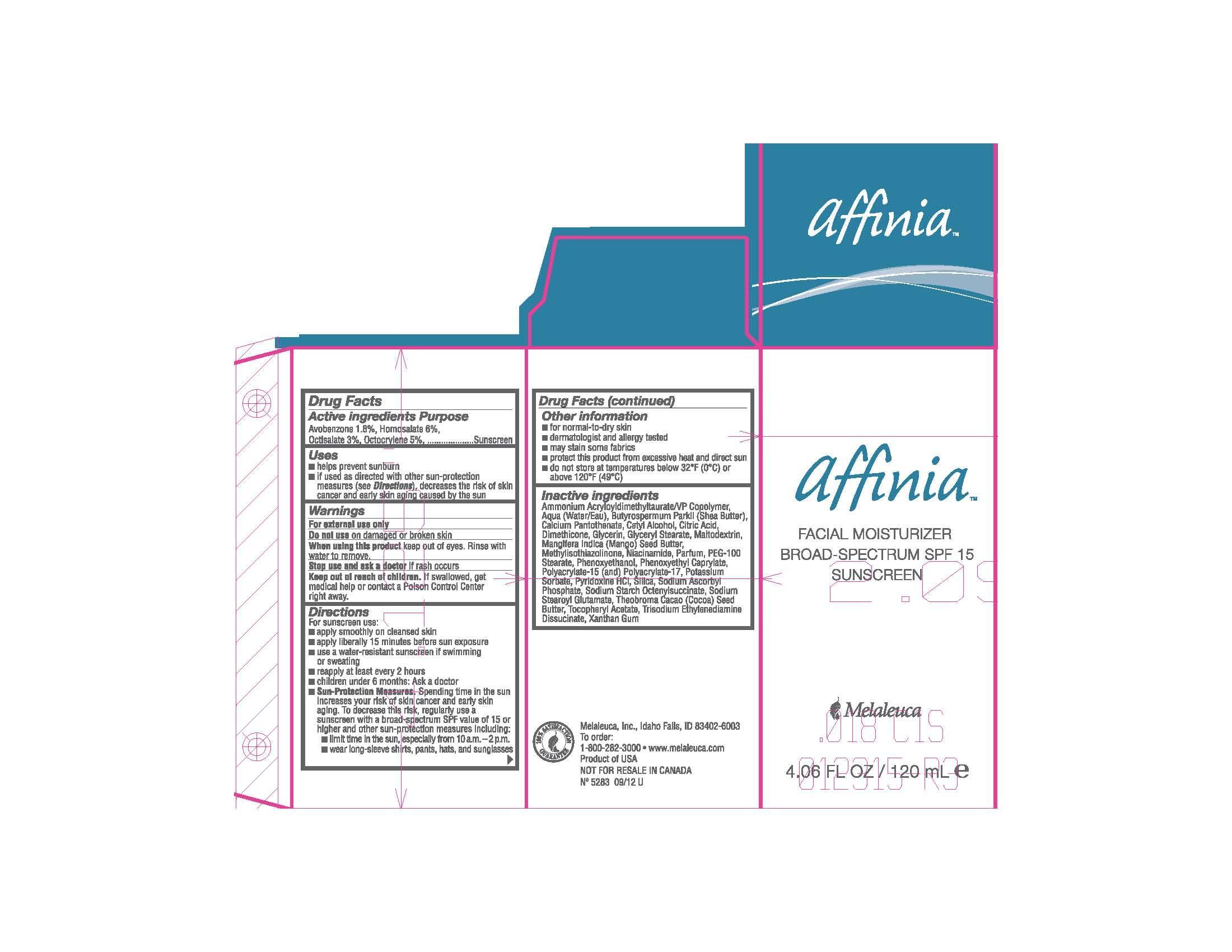 DRUG LABEL: Affinia
NDC: 54473-224 | Form: LOTION
Manufacturer: Melaleuca, Inc.
Category: otc | Type: HUMAN OTC DRUG LABEL
Date: 20230104

ACTIVE INGREDIENTS: HOMOSALATE 7.296 g/120 mL; OCTOCRYLENE 6.08 g/120 mL; OCTISALATE 3.648 g/120 mL; AVOBENZONE 2.1888 g/120 mL
INACTIVE INGREDIENTS: .ALPHA.-TOCOPHEROL ACETATE; AMMONIUM ACRYLOYLDIMETHYLTAURATE/VP COPOLYMER; CALCIUM PANTOTHENATE; CETYL ALCOHOL; CITRIC ACID MONOHYDRATE; COCOA BUTTER; DIMETHICONE; GLYCERIN; GLYCERYL MONOSTEARATE; GLYCERYL STEARATE SE; MALTODEXTRIN; MANGIFERA INDICA SEED BUTTER; METHYLISOTHIAZOLINONE; NIACINAMIDE; PEG-100 STEARATE; PHENOXYETHANOL; PHENOXYETHYL CAPRYLATE; POTASSIUM SORBATE; PYRIDOXINE HYDROCHLORIDE; SHEANUT OIL; SILICON DIOXIDE; SODIUM ASCORBYL PHOSPHATE; SODIUM STEAROYL GLUTAMATE; TRISODIUM ETHYLENEDIAMINE DISUCCINATE; WATER; XANTHAN GUM

Affinia Facial Moisturizer

Active ingredients

Avobenzone 1.8%, Homosalate 6%, Octisalate 3%, Octocrylene 5%

Purpose

Sunscreen

Uses

• helps prevent sunburn

• if used as directed with other sun-protection measures (see Directions), decreases the risk of skin cancer and early skin aging caused by the sun

Warnings

For external use only

Do not use on damaged or broken skin

When using this product keep out of eyes. Rinse with water to remove.

Stop use and ask a doctor is rash occurs.

Keep out of reach of children. If swallowed, get medical help or contact Poison Control Center right away.

Directions

For sunscreen use:

• apply smoothly on cleansed skin

• apply liberally 15 mintues before sun exposure

• use a water-resistant sunscreen if swimming or sweating

• reapply at least every 2 hours

• children under 6 months: Ask a doctor

• Sun-Protection measures. Spending time in the sun increases your risk of skin cancer and early skin aging. To decrease this risk, regularly use a sunscreen with a broad-spectrum SPF value of 15 or higher and other sun-protection measures including: • limit time in the sun, especially from 10a.m.-2p.m. • wear long-sleeve shirts, pants, hats, and sunglasses

Other information

• for normal-to-dry skin

• dermatologist and allergy tested

GENERAL PRECAUTIONS

• may stain some fabrics

STORAGE AND HANDLING

• protect this product from excessive heat and direct sun

• do not store at temperatures below 32°F (0°C) or above 120°F (49°C)

Inactive ingredients

Ammonium Acryloyldimethyltaurate/VP Copolymer, Aqua (Water/Eau), Butyrospermum Parkii (Shea Butter), Calcium Pantothenate, Cetyl Alcohol, Citric Acid, Dimethicone, Glycerin, Glyceryl Stearate, Maltodextrin, Mangifera Indica (Mango) Seed Butter, Methylisothiazolinone, Niacinamide, Parfum, PEG-100 Stearate, Phenoxyethanol, Phenoxyethyl Caprylate, Polyacrylate-15 (and) Polyacrylate-17, Potassium Sorbate, Pyridoxine HCL, Silica, Sodium Ascorbyl Phosphate, Sodium Starch Octenylsuccinate, Sodium Stearoyl Glutamate, Theobroma Cacao (Cocoa) Seed Butter, Tocopheryl Acetate, Trisodium Ethylenediamine Disuccinate, Xanthan Gum